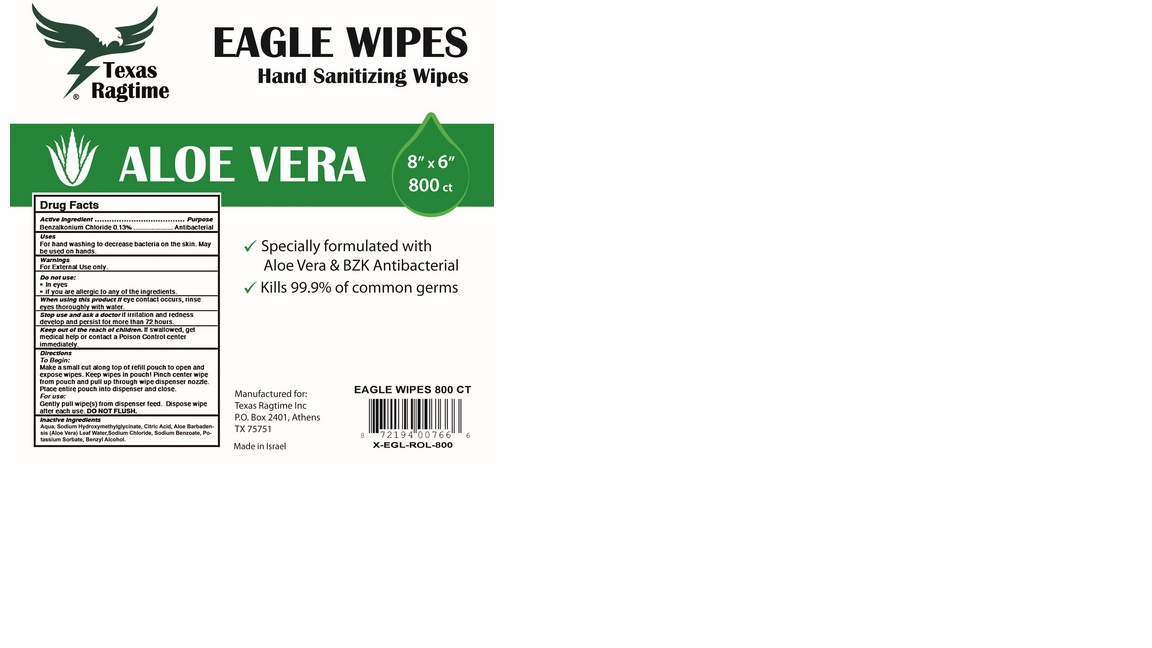 DRUG LABEL: Eagle Wipes Hand Sanitizing Wipes with Aloe Vera
NDC: 76801-972 | Form: SWAB
Manufacturer: TEXAS RAGTIME INC
Category: otc | Type: HUMAN OTC DRUG LABEL
Date: 20230112

ACTIVE INGREDIENTS: BENZALKONIUM CHLORIDE 0.0013 g/1 g
INACTIVE INGREDIENTS: BENZYL ALCOHOL; WATER; POTASSIUM SORBATE; SODIUM BENZOATE; ALOE VERA LEAF; SODIUM CHLORIDE; CITRIC ACID MONOHYDRATE; SODIUM HYDROXYMETHYLGLYCINATE

Eagle Wipes Hand Sanitizing Wipes with Aloe Vera

OTC - Purpose

antimicrobial

Warnings

For External Use only.

Do not use In eyes.

Do not use if you are allergic to any of the ingredients.

When using this product if eye contact occurs, rinse eves thoroughlv with water.

Stop use and ask a doctor if irritation and redness develop and persist for more than 72 hours.

OTC - Do not use

In eyes

If you are allergic to any of the ingredients.

OTC - Keep out of reach of children.

If swallowed, get medical help or contact a Poison Control center immediately.

Dosage and administration

Directions:

To Begin:

Make a small cut along top of refill pouch to open and expose wipes. Keep wipes in pouch. Pinch center wipe from pouch and pull up through wipe dispenser opening. Place entire pouch into dispenser and close.

For use:

Gently pull wipe(s) from dispenser feed. Dispose wipe after each use. DO NOT FLUSH.

OTC - Active Ingredient

Benzalkonium Chloride

Inactive Ingredients

Sodium chloride

Citric acid monohydrate

Water

Sodium acetate

Benzyl alcohol

Sodium Hydroxymethylglycinate

Aloe Vera Leaf

Potassium Sorbate

Indications & Usage

Antibacterial

For hand washing to decrease bacteria on the skin. May be used on hands.

Package label, principal display paneel

Aloe Vera Sanitizing Wipes